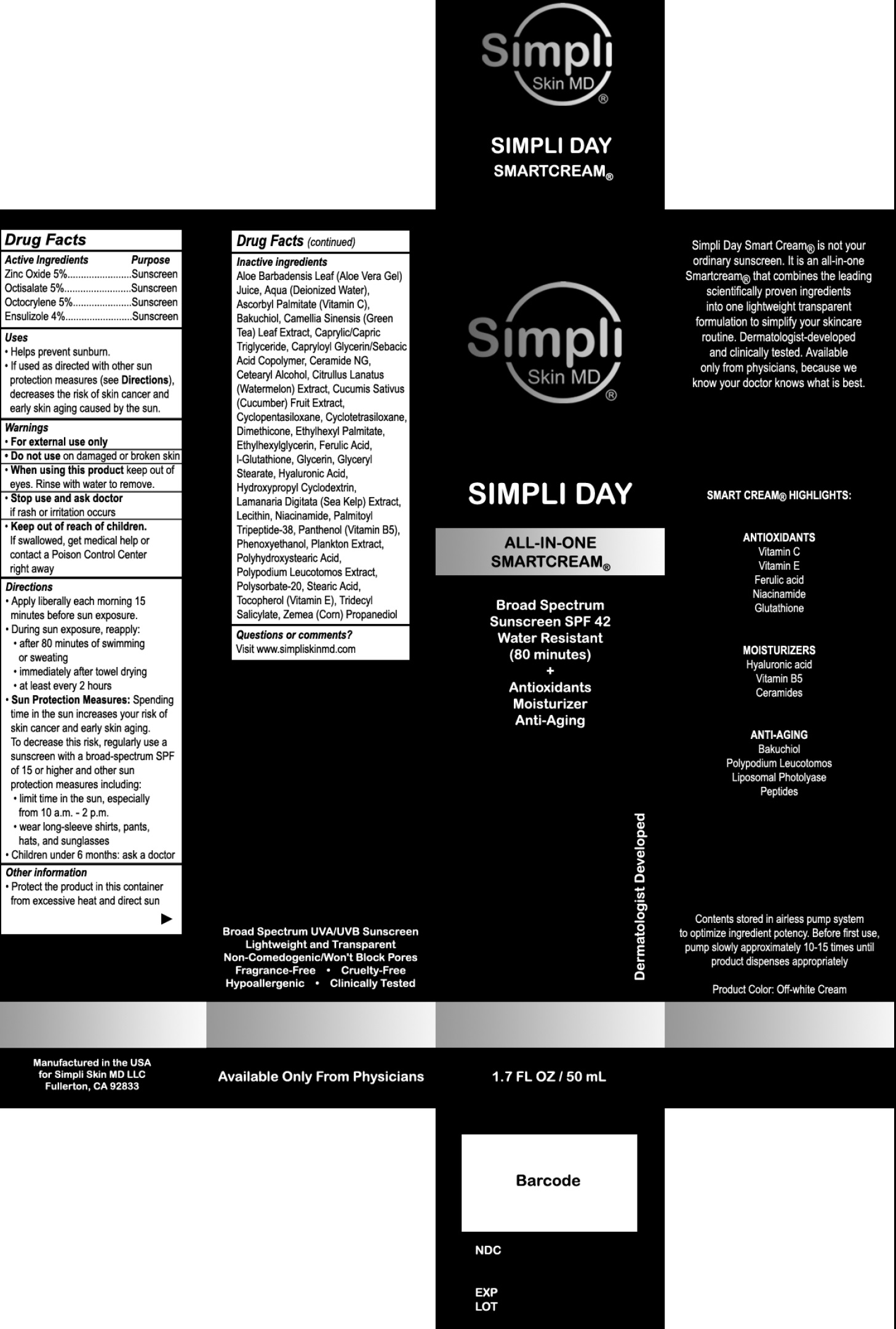 DRUG LABEL: SIMPLI DAY All In One SmartCream SPF 42
NDC: 82733-294 | Form: CREAM
Manufacturer: SIMPLI SKIN MD LLC
Category: otc | Type: HUMAN OTC DRUG LABEL
Date: 20231111

ACTIVE INGREDIENTS: ZINC OXIDE 50 mg/1 mL; OCTISALATE 50 mg/1 mL; OCTOCRYLENE 50 mg/1 mL; ENSULIZOLE 40 mg/1 mL
INACTIVE INGREDIENTS: ALOE VERA LEAF; WATER; ASCORBYL PALMITATE; BAKUCHIOL; GREEN TEA LEAF; MEDIUM-CHAIN TRIGLYCERIDES; CERAMIDE NG; CETOSTEARYL ALCOHOL; WATERMELON; CUCUMBER; CYCLOMETHICONE 5; CYCLOMETHICONE 4; DIMETHICONE; ETHYLHEXYL PALMITATE; ETHYLHEXYLGLYCERIN; FERULIC ACID; GLYCERIN; GLYCERYL MONOSTEARATE; HYALURONIC ACID; LAMINARIA DIGITATA; NIACINAMIDE; PALMITOYL LYSYLDIOXYMETHIONYLLYSINE; PANTHENOL; PHENOXYETHANOL; POLYSORBATE 20; STEARIC ACID; TOCOPHEROL; TRIDECYL SALICYLATE; CORN

SIMPLI DAY: All-In-One SmartCream SPF-42

Active Ingredients

Zinc Oxide 5%

Octisalate 5%

Octocrylene 5%

Ensulizole 4%

Purpose

Sunscreen

Uses

- Helps prevent sunburn.
- If used as directed with other sun protection measures (see), decreases the risk of skin cancer and early skin aging caused by the sun. Directions

Warnings

- For external use only

Do not use

- on damaged or broken skin

When using this product

keep out of eyes. Rinse with water to remove.

Stop use and ask doctor

- if rash or irritation occurs

Keep out of each of children.

If swallowed, get medical help or contact a Poison Control Center right away

Directions

- Apply liberally each morning 15 minutes before sun exposure.
- During sun exposure, reapply:
- after 80 minutes of swimming or sweating
- immediately after towel drying
- at least every 2 hours
- Spending time in the sun increases your risk of skin cancer and early skin aging. To decrease this risk, regularly use a sunscreen with a broad-spectrum SPF of 15 or higher and other sun protection measures including: Sun Protection Measures:
- limit time in the sun, especially from 10 a.m. - 2 p.m.
- wear long-sleeve shirts, pants, hats, and sunglasses
- Children under 6 months: ask a doctor

Other information

- Protect the product in this container from excessive heat and direct sun

Inactive ingredients

Aloe Barbadensis Leaf (Aloe Vera Gel) Juice, Aqua (Deionized Water), Ascorbyl Palmitate (Vitamin C), Bakuchiol, Camellia Sinensis (Green Tea) Leaf Extract, Caprylic/Capric Triglyceride, Capryloyl Glycerin/Sebacic Acid Copolymer, Ceramide NG, Cetearyl Alcohol, Citrullus Lanatus (Watermelon) Extract, Cucumis Sativus (Cucumber) Fruit Extract, Cyclopentasiloxane, Cyclotetrasiloxane, Dimethicone, Ethylhexyl Palmitate, Ethylhexylglycerin, Ferulic Acid, I-Glutathione, Glycerin, Glyceryl Stearate, Hyaluronic Acid, Hydroxypropyl Cyclodextrin, Lamanaria Digitata (Sea Kelp) Extract, Lecithin, Niacinamide, Palmitoyl Tripeptide-38, Panthenol (Vitamin B5), Phenoxyethanol, Plankton Extract, Polyhydroxystearic Acid, Polypodium Leucotomos Extract, Polysorbate-20, Stearic Acid, Tocopherol (Vitamin E), Tridecyl Salicylate, Zemea (Corn) Propanediol

Questions or comments?

Visit www.simpliskinmd.com